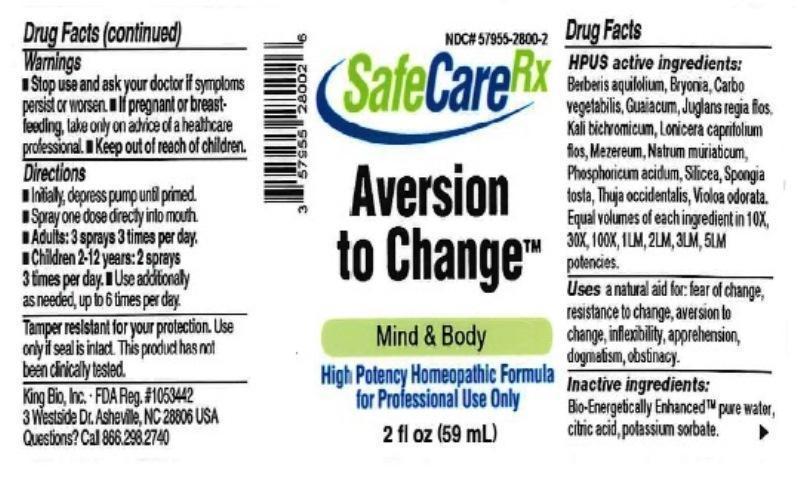 DRUG LABEL: Aversion To Change
NDC: 57955-2800 | Form: LIQUID
Manufacturer: King Bio Inc.
Category: homeopathic | Type: HUMAN OTC DRUG LABEL
Date: 20161115

ACTIVE INGREDIENTS: MAHONIA AQUIFOLIUM ROOT BARK 10 [hp_X]/59 mL; BRYONIA ALBA ROOT 10 [hp_X]/59 mL; ACTIVATED CHARCOAL 10 [hp_X]/59 mL; GUAIACUM OFFICINALE RESIN 10 [hp_X]/59 mL; JUGLANS REGIA FLOWERING TOP 10 [hp_X]/59 mL; POTASSIUM DICHROMATE 10 [hp_X]/59 mL; LONICERA CAPRIFOLIUM FLOWERING TOP 10 [hp_X]/59 mL; DAPHNE MEZEREUM BARK 10 [hp_X]/59 mL; SODIUM CHLORIDE 10 [hp_X]/59 mL; PHOSPHORIC ACID 10 [hp_X]/59 mL; SILICON DIOXIDE 10 [hp_X]/59 mL; SPONGIA OFFICINALIS SKELETON, ROASTED 10 [hp_X]/59 mL; THUJA OCCIDENTALIS LEAFY TWIG 10 [hp_X]/59 mL; VIOLA ODORATA 10 [hp_X]/59 mL
INACTIVE INGREDIENTS: ANHYDROUS CITRIC ACID; POTASSIUM SORBATE; WATER

Aversion to Change

ACTIVE INGREDIENT

Drug Facts__________________________________________________________________________________________________________

HPUS active ingredients: Berberis aquifolium, Bryonia, Carbo vegetabilis, Guaiacum, Juglans regia, flos, Kali bichromicum, Lonicera caprifolium, flos, Mezereum, Natrum muriaticum, Phosphoricum acidum, Silicea, Spongia tosta, Thuja occidentalis, Viola odorata. Equal volumes of each ingredient in 10X, 30X, 100X, 1LM, 2LM, 3LM, 5LM potencies.

INDICATIONS AND USAGE

Uses a natural aid for: fear of change, resistance to change, aversion to change, inflexibility, apprehension, dogmatism, obstinacy.

Inactive Ingredients:

Bio-Energetically Enhanced™ pure water, citric acid and potassium sorbate.

Warnings

- Stop use and ask your doctor if symptoms persist or worsen.
- If pregnant or breast-feeding, take only on advice of a healthcare professional.

- Keep out of reach of children.

Directions

- Initially, depress pump until primed.
- Spray one dose directly into mouth.
- Adults: 3 sprays 3 times per day
- Children 2-12 years: 2 sprays 3 times per day.
- Use additionally as needed, up to 6 times per day.

OTHER SAFETY INFORMATION

Tamper resistant for your protection. Use only if safety seal is intact. This product has not been clinically tested.

PURPOSE

Uses a natural aid for:

- fear of change
- resistance to change
- aversion to change
- inflexibility
- apprehension
- dogmatism
- obstinacy